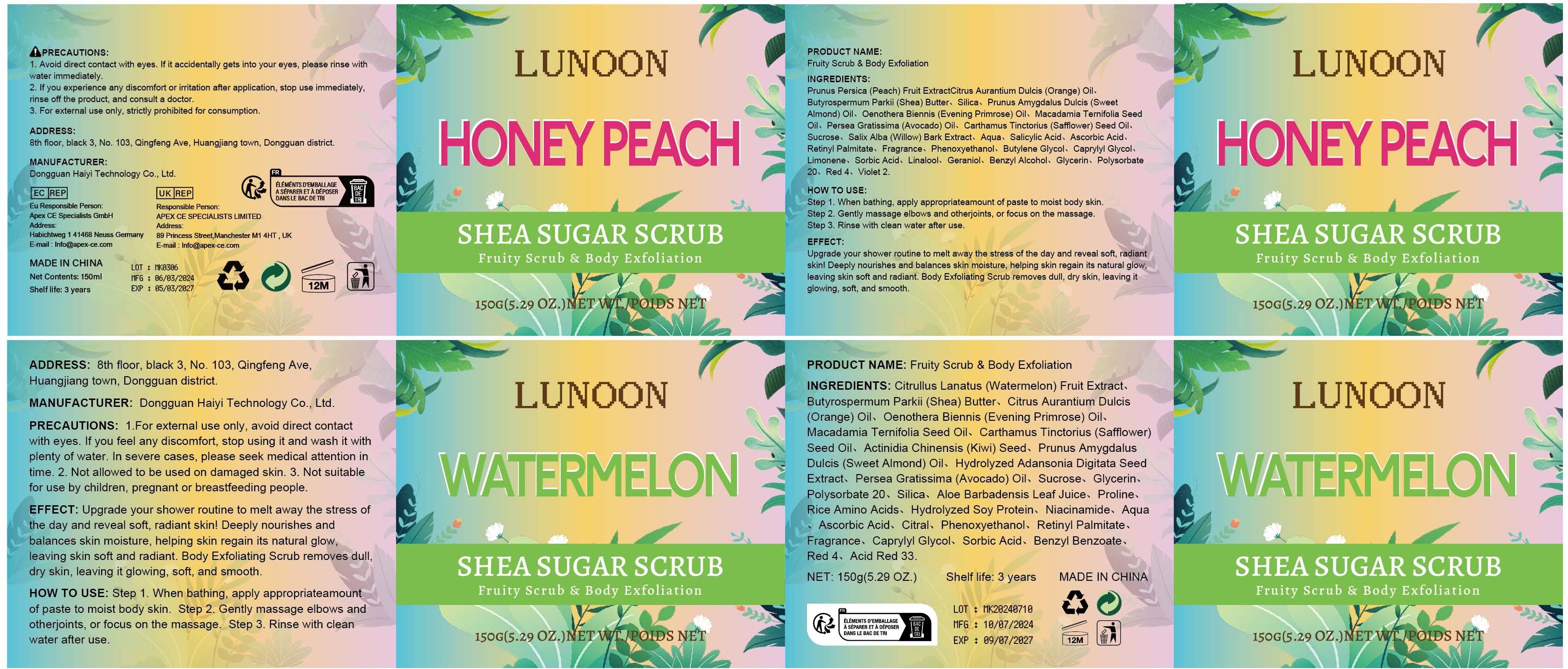 DRUG LABEL: Fruity Scrub Body Exfoliation
NDC: 84732-094 | Form: PASTE
Manufacturer: Dongguan Haiyi Technology Co.,Ltd.
Category: otc | Type: HUMAN OTC DRUG LABEL
Date: 20241120

ACTIVE INGREDIENTS: SILICON DIOXIDE 1 mg/100 g
INACTIVE INGREDIENTS: OENOTHERA BIENNIS (EVENING PRIMROSE) OIL; CARTHAMUS TINCTORIUS (SAFFLOWER) SEED OIL; MACADAMIA TERNIFOLIA SEED OIL; PRUNUS AMYGDALUS DULCIS (SWEET ALMOND) OIL; PRUNUS PERSICA (PEACH) FRUIT EXTRACT; BUTYROSPERMUM PARKII (SHEA) BUTTER; CITRUS AURANTIUM DULCIS (ORANGE) OIL; CITRULLUS LANATUS (WATERMELON) FRUIT EXTRACT

Active ingredient

Silica

Inactive ingredient

CITRULLUS LANATUS(WATERMELON) FRUIT EXTRACT

BUTYROSPERMUM PARKII (SHEA) BUTTER

CITRUS AURANTIUM DULCIS (ORANGE) OIL

OENOTHERA BIENNIS (EVENING PRIMROSE) OIL

MACADAMIA TERNIFOLIA SEED OIL

CARTHAMUS TINCTORIUS (SAFFLOWER) SEED OIL

PRUNUS PERSICA (PEACH) FRUIT EXTRACT

PRUNUS AMYGDALUS DULCIS(SWEET ALMOND) OIL

Purpose section

Upgrade your shower routine to melt away the stress of the day and reveal soft, radiantskin! Deeply nourishes and balances skin moisture, helping skin regain its natural glow,leaving skin soft and radiant. Body Exfoliating Scrub removes dull, dry skin, leaving it glowing, soft, and smooth.

Warning

1. Avoid direct contact with eyes. lf it accidentally gets into your eyes, please rinse withwater immediately.

2. lf you experience any discomfort or irritation after application, stop use immediately.rinse off the product, and consult a doctor.

3. For external use only, strictly prohibited for consumption.

stop use

This product may cause allergic reactions in asmall number of people.
lf youexperience any discomfort,please stop using it immediately.

not use

Not suitable for use by children, pregnantor breast feeding people.

OUT OF CHILDREN

KEEP THE PRODUCT OUT OF REACH OF CHILDREN to

HOW TO USE

Step 1. When bathing, apply appropriateamount of paste to moist body skin.
Step 2. Gently massage elbows and otherjoints, or focus on the massage.
Step 3. Rinse with clean water after use.

Dosage

take an appropriateamount,Use 2-3 times a week